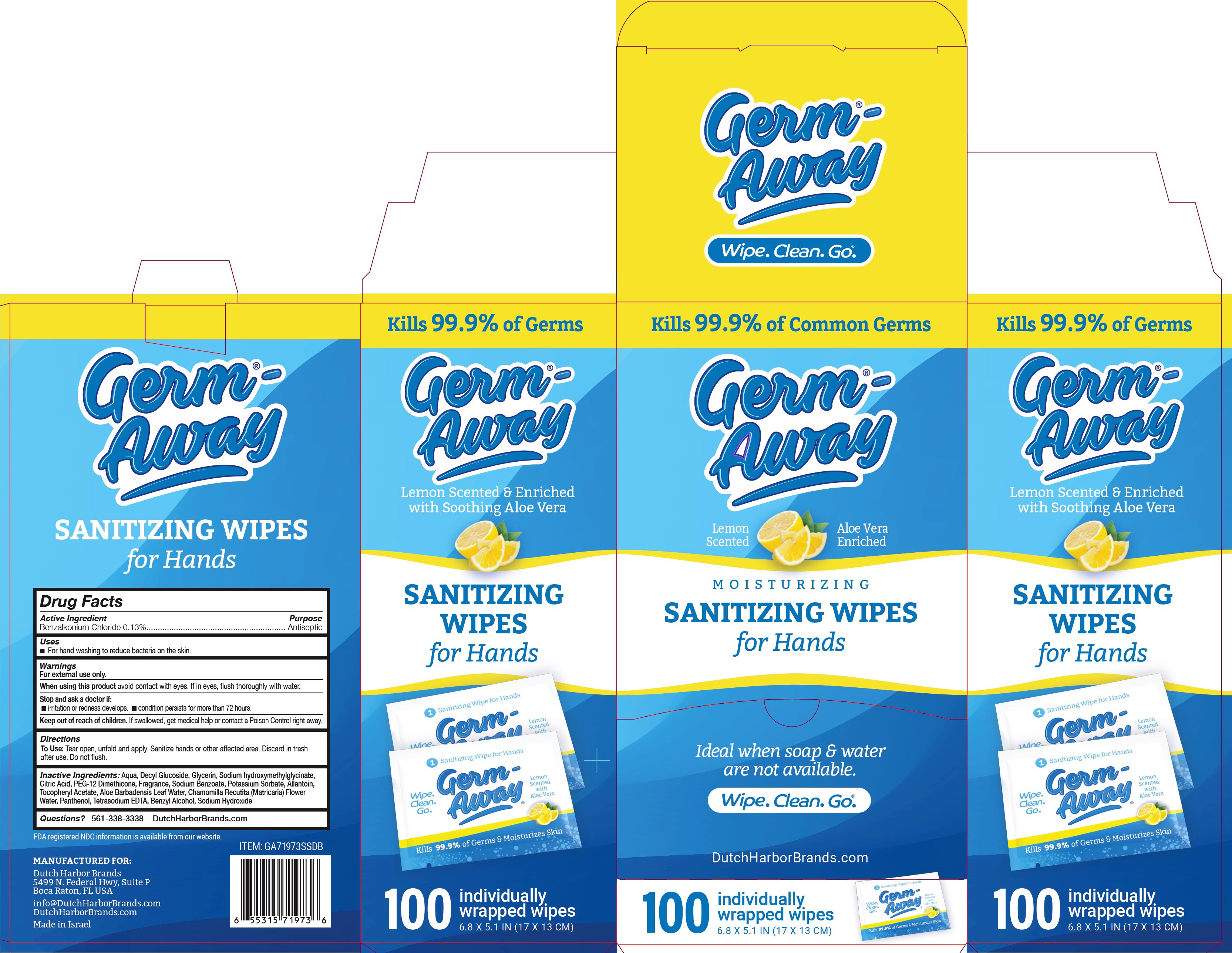 DRUG LABEL: Germ-Away
NDC: 74680-108 | Form: CLOTH
Manufacturer: Unico International Trading Corp
Category: otc | Type: HUMAN OTC DRUG LABEL
Date: 20260108

ACTIVE INGREDIENTS: BENZALKONIUM CHLORIDE 1.3 mg/1 g
INACTIVE INGREDIENTS: TETRAHYDROLINALOOL; 3,7-DIMETHYL-1-OCTANOL; 2,2'-OXYDIPROPANOL; DIPHENYL ETHER; ANHYDROUS CITRIC ACID; EUCALYPTOL; COUMARIN; PEG-12 DIMETHICONE (300 CST); .ALPHA.-TOCOPHEROL ACETATE; CHAMOMILE; ALLANTOIN; PANTHENOL; ALOE VERA LEAF; GLYCERIN; DECYL GLUCOSIDE; POTASSIUM SORBATE; SODIUM BENZOATE; WATER; EDETATE SODIUM; SODIUM HYDROXYMETHYLGLYCINATE; CP FORMATE

Germ-Away

Active Ingredient

Benzalkonium chloride 0.13%

Keep out of the reach of children, except with adult supervision.

Warrning section

Warning section - for external use only. Do not use in the eyes. Keep out of eyes. In case of eye contact rinse with water. If irritation develops, just continue use. Consult doctor if your condition persists for more than 72 hours. If swallowed, seek medical attention or contact a Poison Control Center.

To use

Tear open, unfold and apply. Sanitize hands or other affected area. Discard in trash after use. Do not flush. Close lid flap after use to retain moisture.

Purpose

Anti-bacterial

Indications and Usage

Sanitize hands or other affected area.

Inactive Ingredients

Aqua, Decyl Glucoside, Glycerin, Sodium Hydroxymethylglycinate, Citric Acid, PEG-12 Dimethicone Copolyol, Tetrasodium EDTA, Potassium Sorbate, Sodium Benzoate, Aloe Barbadensis Leaf Extract, Chamomilla Recutita (Matricaria) Flower Extract, Allantoin, Panthenol, Tocopheryl Acetate, fragrance